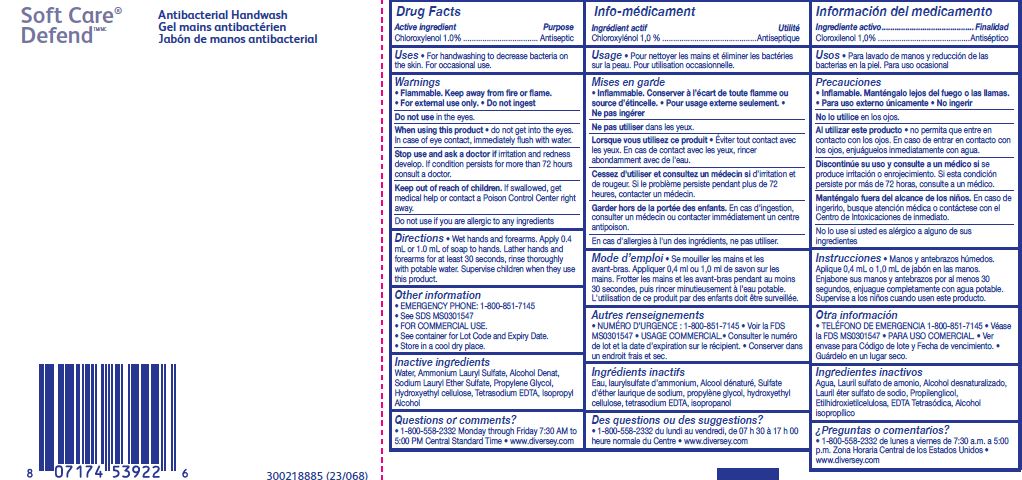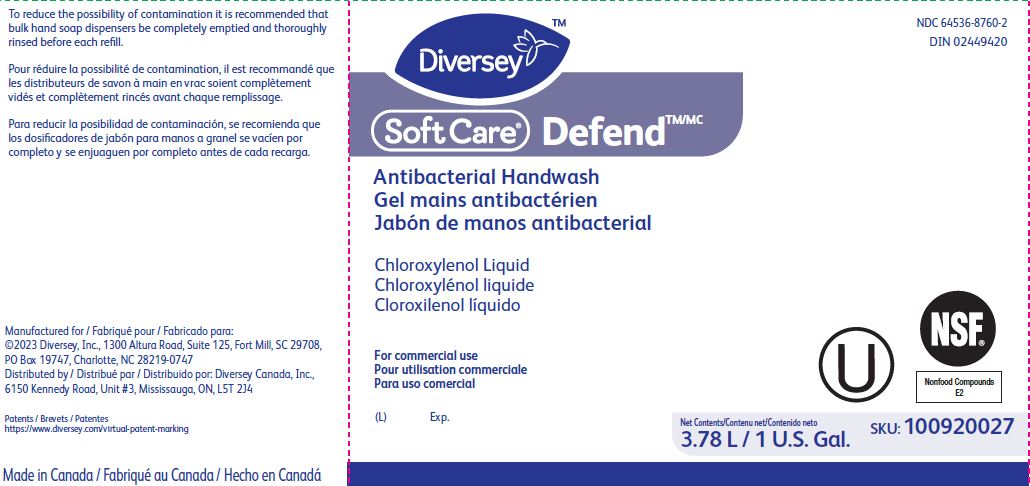 DRUG LABEL: Soft Care Defend Antibacterial Handwash
NDC: 64536-8760 | Form: SOLUTION
Manufacturer: Diversey, Inc.
Category: otc | Type: HUMAN OTC DRUG LABEL
Date: 20241216

ACTIVE INGREDIENTS: CHLOROXYLENOL 10 g/1 L
INACTIVE INGREDIENTS: SODIUM LAURETH-3 SULFATE; WATER; ALCOHOL; PROPYLENE GLYCOL; AMMONIUM LAURYL SULFATE; HYDROXYETHYL CELLULOSE (2000 MPA.S AT 1%); ISOPROPYL ALCOHOL; EDETATE SODIUM

Drug Facts

Active ingredient

Chloroxylenol 1.0%

Purpose

Antiseptic

Uses

For handwashing to decrease bacteria on the skin.

For occasional use.

Warnings

Flammable.

Keep away from fire or flame.

For external use only.

Do not ingest

Do not use in the eyes.

When using this product do not get into the eyes.

In case of eye contact, immediately flush with water.

Stop use and ask a doctor if irritation and redness develop.

If condition persists for more than 72 hours consult a doctor.

Keep out of reach of children.

If swallowed, get medical help or contact a Poison Control Center right away.

Do not use if you are allergic to any ingredients

Directions

Wet hands and forearms.

Apply 0.4 mL or 1.0 mL of soap to hands.

Lather hands and forearms for at least 30 seconds, rinse thoroughly with potable water.

Supervise children when they use this product.

Other information

EMERGENCY PHONE: 1-800-851-7145

See SDS MS0301547

FOR COMMERCIAL USE.

See container for Lot Code and Expiry Date.

Store in a cool dry place.

Inactive ingredients

Water, Ammonium Lauryl Sulfate, Alcohol Denat, Sodium Lauryl Ether Sulfate, Propylene Glycol, Hydroxyethyl cellulose, Tetrasodium EDTA, Isopropyl Alcohol

Questions or comments?

1-800-558-2332 Monday through Friday 7:30 AM to 5:00 PM Central Standard Time

www.diversey.com

Directions

Wet hands and forearms.

Apply 0.4 mLor 1.0 mL of soap to hands.

Lather hands and forearmsfor at least 30 seconds, rinse thoroughly with potable water.

Supervise children when they use this product.

PACKAGE LABEL

NDC 64536-8760-2

DIN 02449420

Diversey

SoftCare Defend

Antibacterial Handwash

Chloroxylenol Liquid

For comercial use

U

NSF

Nonfood Compounds

E2

(L) Exp.

Net Contents

3.78 L/1 U.S. Gal.

SKU: 100920027